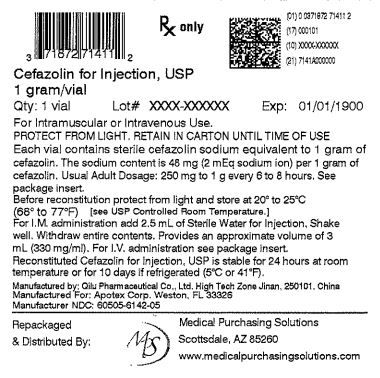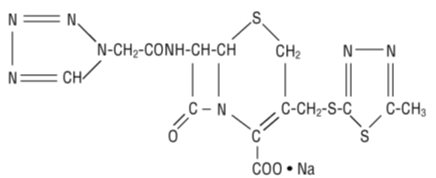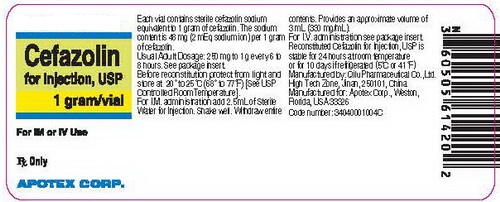 DRUG LABEL: Cefazolin
NDC: 71872-7141 | Form: INJECTION, POWDER, FOR SOLUTION
Manufacturer: Medical Purchasing Solutions, LLC
Category: prescription | Type: HUMAN PRESCRIPTION DRUG LABEL
Date: 20230516

ACTIVE INGREDIENTS: CEFAZOLIN SODIUM 1 g/1 1

HIGHLIGHTS OF PRESCRIBING INFORMATION

These highlights do not include all the information needed to use CEFAZOLIN FOR INJECTION safely and effectively. See full prescribing information for CEFAZOLIN FOR INJECTION.
CEFAZOLIN for injection, for intravenous use
Initial U.S. Approval: 1973
To reduce the development of drug-resistant bacteria and maintain the effectiveness of cefazolin for injection and other antibacterial drugs, cefazolin for injection should be used only to treat or prevent infections that are proven or strongly suspected to be caused by bacteria.

1 INDICATIONS AND USAGE

Cefazolin for Injection, USP is a cephalosporin antibacterial indicated in the treatment of the following infections caused by susceptible isolates of the designated microorganisms:

- Respiratory tract infections. (1.1)
- Urinary tract infections. (1.2)
- Skin and skin structure infections. (1.3)
- Biliary tract infections. (1.4)
- Bone and joint infections. (1.5)
- Genital infections. (1.6)
- Septicemia. (1.7)
- Endocarditis. (1.8)
- Perioperative prophylaxis. (1.9)

2 DOSAGE AND ADMINISTRATION

For intravenous or intramuscular use. (2)

Recommended Dosing Schedule in Adult Patients with CrCl Greater Than or Equal to 55 mL/min. (2.1)
Site and Type of Infection | Dose | Frequency
Moderate to severe infections | 500 mg to 1 gram | every 6 to 8 hours
Mild infections caused by susceptible gram-positive cocci | 250 mg to 500 mg | every 8 hours
Acute, uncomplicated urinary tract infections | 1 gram | every 12 hours
Pneumococcal pneumonia | 500 mg | every 12 hours
Severe, life-threatening infections (e.g., endocarditis, septicemia) [In rare instances, doses of up to 12 grams of cefazolin per day have been used.] | 1 gram to 1.5 grams | every 6 hours

3 DOSAGE FORMS AND STRENGTHS

- 1 g per vial.(3)

4 CONTRAINDICATIONS

- Hypersensitivity to cefazolin or other cephalosporin class antibacterial drugs, penicillins, or other beta-lactams. (4.1)

5 WARNINGS AND PRECAUTIONS

- Hypersensitivity Reactions: Cross-hypersensitivity may occur in up to 10% of patients with a history of penicillin allergy. If an allergic reaction occurs, discontinue the drug. (5.1)
- Use in Patients with Renal Impairment: Dose adjustment required for patients with CrCl less than 55 mL/min. (5.2)
- Clostridium difficile-associated Diarrhea: May range from mild diarrhea to fatal colitis. Evaluate if diarrhea occurs. (5.3)

6 ADVERSE REACTIONS

- Most Common Adverse Reactions: Gastrointestinal (nausea, vomiting, diarrhea), and allergic reactions (anaphylaxis, urticaria, skin rash). (6)

To report SUSPECTED ADVERSE REACTIONS, contact Apotex Corp. at 1-800-706-5575 or FDA at 1-800-FDA-1088 or www.fda.gov/medwatch.

7 DRUG INTERACTIONS

- Probenecid: May decrease renal tubular secretion of cephalosporins when used concurrently, resulting in increased and more prolonged cephalosporin blood concentrations. (7)

8 USE IN SPECIFIC POPULATIONS

- Pediatric Use: Safety and effectiveness for use in premature infants and neonates have not been established. See Dosage and Administration (2.4) for recommended dosage in pediatric patients older than 1 month. (8.4)
- Renal Impairment: Lower daily dosage of cefazolin for injection is required in patients with impaired renal function (creatinine clearance less than 55 mL/min). (8.6)

FULL PRESCRIBING INFORMATION

1 INDICATIONS AND USAGE

To reduce the development of drug-resistant bacteria and maintain the effectiveness of Cefazolin for Injection, USP and other antibacterial drugs, Cefazolin for Injection, USP should be used only to treat or prevent infections that are proven or strongly suspected to be caused by susceptible bacteria. When culture and susceptibility information are available, they should be considered in selecting or modifying antibacterial therapy. In the absence of such data, local epidemiology and susceptibility patterns may contribute to the empiric selection of therapy.

Cefazolin for Injection, USP is indicated for the treatment of the following serious infections due to susceptible organisms.

1.1 Respiratory Tract Infections

Respiratory tract infections due to Streptococcus pneumoniae, Klebsiella species, H. influenzae, Staphylococcus aureus (penicillin-sensitive and penicillin-resistant), and group A beta-hemolytic streptococci.

Injectable benzathine penicillin is considered to be the drug of choice in treatment and prevention of streptococcal infections, including the prophylaxis of rheumatic fever.

Cefazolin for Injection is effective in the eradication of streptococci from the nasopharynx; however, data establishing the efficacy of Cefazolin for Injection in the subsequent prevention of rheumatic fever are not available at present.

1.2 Urinary Tract Infections

Urinary tract infections due to Escherichia coli, and Proteus mirabilis, Klebsiella species, and some strains of enterobacter and enterococci.

1.3 Skin and Skin Structure Infections

Skin and skin structure infections due to S. aureus (penicillin-sensitive and penicillin-resistant), group A beta-hemolytic streptococci, and other strains of streptococci.

1.4 Biliary Tract Infections

Biliary infections due to E. coli, various strains of streptococci, P. mirabilis, Klebsiella species, and S. aureus.

1.5 Bone and Joint Infections

Bone and joint infections due to S. aureus.

1.6 Genital Infections

Genital infections due to E. coli, and P. mirabilis, Klebsiella species, and some strains of enterococci.

1.7 Septicemia

Septicemia due to S. pneumoniae, S. aureus (penicillin-sensitive and penicillin-resistant), P. mirabilis, E. coli, and Klebsiella species.

1.8 Endocarditis

Endocarditis due to S. aureus (penicillin-sensitive and penicillin-resistant) and group A beta-hemolytic streptococci.

1.9 Perioperative Prophylaxis

The prophylactic administration of Cefazolin for Injection preoperatively, intraoperatively, and postoperatively may reduce the incidence of certain postoperative infections in patients undergoing surgical procedures which are classified as contaminated or potentially contaminated (e.g., vaginal hysterectomy, and cholecystectomy in high-risk patients such as those older than 70 years, with acute cholecystitis, obstructive jaundice, or common duct bile stones).

The perioperative use of Cefazolin for Injection may also be effective in surgical patients in whom infection at the operative site would present a serious risk (e.g., during open-heart surgery and prosthetic arthroplasty).

If there are signs of infection, specimens for cultures should be obtained for the identification of the causative organism so that appropriate therapy may be instituted [ see Dosage and Administration (2.1)].

2 DOSAGE AND ADMINISTRATION

2.1 Adult Population

The recommended adult dosages are outlined in Table 1. Cefazolin for Injection should be administered intravenously (IV) or intramuscularly (IM).

Table 1: Recommended Dosing Schedule in Adult Patients with CrCl Greater Than or Equal to 55 mL/min.
Site and Type of Infection | Dose | Frequency
Moderate to severe infections | 500 mg to 1 gram | every 6 to 8 hours
Mild infections caused by susceptible gram-positive cocci | 250 mg to 500 mg | every 8 hours
Acute, uncomplicated urinary tract infections | 1 gram | every 12 hours
Pneumococcal pneumonia | 500 mg | every 12 hours
Severe, life-threatening infections (e.g., endocarditis, septicemia) [In rare instances, doses of up to 12 grams of cefazolin per day have been used.] | 1 gram to 1.5 grams | every 6 hours

2.2 Perioperative Prophylactic Use

To prevent postoperative infection in contaminated or potentially contaminated surgery, recommended doses are:

- 1 gram IV or IM administered 1/2 hour to 1 hour prior to the start of surgery.
- For lengthy operative procedures (e.g., 2 hours or more), 500 mg to 1 gram IV or IM during surgery (administration modified depending on the duration of the operative procedure).
- 500 mg to 1 gram IV or IM every 6 to 8 hours for 24 hours postoperatively.

It is important that (i) the preoperative dose be given just prior (1/2 hour to 1 hour) to the start of surgery so that adequate antibiotic levels are present in the serum and tissues at the time of initial surgical incision; and (ii) Cefazolin for Injection be administered, if necessary, at appropriate intervals during surgery to provide sufficient levels of the antibiotic drug at the anticipated moments of greatest exposure to infective organisms.

The prophylactic administration of cefazolin should usually be discontinued within a 24-hour period after the surgical procedure. In surgery where the occurrence of infection may be particularly devastating (e.g., open-heart surgery and prosthetic arthroplasty), the prophylactic administration of cefazolin may be continued for 3 to 5 days following the completion of surgery.

2.3 Patients with Renal Impairment

Cefazolin for Injection may be used in patients with reduced renal function with the following dosage adjustments outlined in Table 2. Patients with a creatinine clearance of 55 mL/min. or greater or a serum creatinine of 1.5 mg % or less can be given full doses. Patients with creatinine clearance rates of 35 to 54 mL/min. or serum creatinine of 1.6 to 3.0 mg % can also be given full doses but dosage should be restricted to at least 8 hour intervals. Patients with creatinine clearance rates of 11 to 34 mL/min. or serum creatinine of 3.1 to 4.5 mg % should be given 1/2 the usual dose every 12 hours. Patients with creatinine clearance rates of 10 mL/min. or less or serum creatinine of 4.6 mg % or greater should be given 1/2 the usual dose every 18 to 24 hours. All reduced dosage recommendations apply after an initial loading dose appropriate to the severity of the infection. Patients undergoing peritoneal dialysis: [ see Clinical Pharmacology (12.3)].

Table 2: Dosage Adjustment for Patients with Renal Impairment
Creatinine Clearance | Dose | Frequency
55 mL/min. or greater | full dose | normal frequency
35 to 54 mL/min. | full dose | every 8 hours or longer
11 to 34 mL/min. | 1/2 usual dose | every 12 hours
10 mL/min. or less | 1/2 usual dose | every 18 to 24 hours

2.4 Pediatric Population

In pediatric patients, a total daily dosage of 25 to 50 mg per kg (approximately 10 to 20 mg per pound) of body weight, divided into 3 or 4 equal doses, is effective for most mild to moderately severe infections. Total daily dosage may be increased to 100 mg per kg (45 mg per pound) of body weight for severe infections. Since safety for use in premature infants and in neonates has not been established, the use of cefazolin for injection in these patients is not recommended.

Pediatric Dosage Guide

Weight |  | 25 mg/kg/Day Divided into 3 Doses |  | 25 mg/kg/Day Divided into 4 Doses
Lbs | Kg | Approximate Single Dose mg/q8h | Vol. (mL) needed with dilution of 125 mg/mL | Approximate Single Dose mg/q6h | Vol. (mL) needed with dilution of 125 mg/mL
10 | 4.5 | 40 mg | 0.35 mL | 30 mg | 0.25 mL
20 | 9 | 75 mg | 0.6 mL | 55 mg | 0.45 mL
30 | 13.6 | 115 mg | 0.9 mL | 85 mg | 0.7 mL
40 | 18.1 | 150 mg | 1.2 mL | 115 mg | 0.9 mL
50 | 22.7 | 190 mg | 1.5 mL | 140 mg | 1.1 mL

Weight |  | 50 mg/kg/Day Divided into 3 Doses |  | 50 mg/kg/Day Divided into 4 Doses
Lbs | Kg | Approximate Single Dose mg/q8h | Vol. (mL) needed with dilution of 225 mg/mL | Approximate Single Dose mg/q6h | Vol. (mL) needed with dilution of 225 mg/mL
10 | 4.5 | 75 mg | 0.35 mL | 55 mg | 0.25 mL
20 | 9 | 150 mg | 0.7 mL | 110 mg | 0.5 mL
30 | 13.6 | 225 mg | 1 mL | 170 mg | 0.75 mL
40 | 18.1 | 300 mg | 1.35 mL | 225 mg | 1 mL
50 | 22.7 | 375 mg | 1.7 mL | 285 mg | 1.25 mL

In pediatric patients with mild to moderate renal impairment (creatinine clearance of 70 to 40 mL/min.), 60 percent of the normal daily dose given in equally divided doses every 12 hours should be sufficient. In patients with moderate impairment (creatinine clearance of 40 to 20 mL/min.), 25 percent of the normal daily dose given in equally divided doses every 12 hours should be adequate. Pediatric patients with severe renal impairment (creatinine clearance of 20 to 5 mL/min.) may be given 10 percent of the normal daily dose every 24 hours. All dosage recommendations apply after an initial loading dose.

2.5 Preparation of Parenteral Solution

Parenteral drug products should be SHAKEN WELL when reconstituted, and inspected visually for particulate matter prior to administration. If particulate matter is evident in reconstituted fluids, the drug solutions should be discarded.

When reconstituted or diluted according to the instructions below, Cefazolin for Injection is stable for 24 hours at room temperature or for 10 days if stored under refrigeration (5°C or 41°F). Reconstituted solutions may range in color from pale yellow to yellow without a change in potency.

Single-Dose Vials

For IM injection, IV direct (bolus) injection or IV infusion, reconstitute with Sterile Water for Injection according to the following table. SHAKE WELL.

Vial Size | Amount of Diluent | Approximate Concentration | Approximate Available Volume
1 g | 2.5 mL | 330 mg/mL | 3 mL

2.6 Intramuscular Administration

Reconstitute vials with Sterile Water for Injection according to the dilution table above. Shake well until dissolved. Cefazolin should be injected into a large muscle mass. Pain on injection is infrequent with Cefazolin for Injection.

2.7 Intravenous Administration

Direct (bolus) injection: Following reconstitution according to the above table, further dilute vials with approximately 5 mL Sterile Water for Injection. Inject the solution slowly over 3 to 5 minutes, directly or through tubing for patients receiving parenteral fluids (see list below).

Intermittent or continuous infusion: Dilute reconstituted Cefazolin for Injection in 50 to 100 mL of 1 of the following solutions:

Sodium Chloride Injection, USP
5% or 10% Dextrose Injection, USP
5% Dextrose in Lactated Ringer’s Injection, USP
5% Dextrose and 0.9% Sodium Chloride Injection, USP
5% Dextrose and 0.45% Sodium Chloride Injection, USP
5% Dextrose and 0.2% Sodium Chloride Injection, USP
Lactated Ringer’s Injection, USP
Invert Sugar 5% or 10% in Sterile Water for Injection
Ringer’s Injection, USP
5% Sodium Bicarbonate Injection, USP

Prior to administration parenteral drug products should be inspected visually for particulate matter and discoloration whenever solution and container permit.

3 DOSAGE FORMS AND STRENGTHS

Single-dose vials:

- 1 g Cefazolin for Injection

4 CONTRAINDICATIONS

4.1 Hypersensitivity to Cefazolin or the Cephalosporin Class of Antibacterial Drugs, Penicillins, or Other Beta-lactams

Cefazolin for injection is contraindicated in patients who have a history of immediate hypersensitivity reactions (e.g., anaphylaxis, serious skin reactions) to cefazolin or the cephalosporin class of antibacterial drugs, penicillins, or other beta-lactams [ see Warnings and Precautions (5.1)].

5 WARNINGS AND PRECAUTIONS

5.1 Hypersensitivity Reactions to Cefazolin, Cephalosporins, Penicillins, or Other Beta-lactams

Before therapy with Cefazolin for Injection is instituted, careful inquiry should be made to determine whether the patient has had previous hypersensitivity reactions to cefazolin, cephalosporins, penicillins, or other drugs. If this product is given to penicillin-sensitive patients, caution should be exercised because cross-hypersensitivity among beta-lactam antibiotics has been clearly documented and may occur in up to 10% of patients with a history of penicillin allergy. If an allergic reaction to Cefazolin for Injection occurs, discontinue treatment with the drug. Serious acute hypersensitivity reactions may require treatment with epinephrine and other emergency measures, including oxygen, IV fluids, IV antihistamines, corticosteroids, pressor amines, and airway management, as clinically indicated.

5.2 Use in Patients with Renal Impairment

As with other β-lactam antibiotics, seizures may occur if inappropriately high doses are administered to patients with impaired renal function (creatinine clearance less than 55 mL/min.) [ see Dosage and Administration (2.3)].

5.3 Clostridium difficile-associated Diarrhea

Clostridium difficile-associated diarrhea (CDAD) or pseudomembranous colitis has been reported with nearly all antibacterial agents, including cefazolin, and may range in severity from mild to life-threatening. Therefore, it is important to consider this diagnosis in patients who present with diarrhea subsequent to the administration of antibacterial agents.

Treatment with antibacterial agents alters the normal flora of the colon and may permit overgrowth of clostridia. Studies indicate that a toxin produced by Clostridium difficile is a primary cause of “antibiotic-associated colitis.”

Cefazolin for Injection, as with all cephalosporins, should be prescribed with caution in individuals with a history of gastrointestinal disease, particularly colitis.

After the diagnosis of CDAD or pseudomembranous colitis has been established, therapeutic measures should be initiated. Mild cases of pseudomembranous colitis usually respond to drug discontinuation alone. In moderate to severe cases, consideration should be given to management with fluids and electrolytes, protein supplementation, and treatment with an oral antibacterial drug clinically effective against C. difficile colitis.

5.4 Risk of Development of Drug-resistant Bacteria

Prescribing cefazolin in the absence of a proven or strongly suspected bacterial infection or a prophylactic indication is unlikely to provide benefit to the patient and increases the risk of the development of drug-resistant bacteria.

As with other antimicrobials, prolonged use of cefazolin for injection may result in overgrowth of nonsusceptible microorganisms. Repeated evaluation of the patient's condition is essential. Should superinfection occur during therapy, appropriate measures should be taken.

5.5 Drug/Laboratory Test Interactions

Urinary Glucose

The administration of cefazolin may result in a false-positive reaction with glucose in the urine when using CLINITEST® tablets. It is recommended that glucose tests based on enzymatic glucose oxidase reactions (e.g., CLINISTIX®) be used.

Coombs’ Test

Positive direct Coombs' tests have been reported during treatment with cefazolin. In hematologic studies or in transfusion cross-matching procedures when antiglobulin tests are performed on the minor side or in Coombs' testing of newborns whose mothers have received cephalosporin antibacterial drugs before parturition, it should be recognized that a positive Coombs' test may be due to the drug.

6 ADVERSE REACTIONS

The following reactions have been reported:

- Hypersensitivity reactions [ see Warnings and Precautions (5.1)]
- Clostridium difficile-associated diarrhea [ see Warnings and Precautions (5.3)]

6.1 Clinical Trials Experience

The following adverse reactions were reported from clinical trials:

Gastrointestinal: Diarrhea, oral candidiasis (oral thrush), vomiting, nausea, stomach cramps, anorexia, and pseudomembranous colitis. Onset of pseudomembranous colitis symptoms may occur during or after antibiotic treatment [ see Warnings and Precautions (5.3)]. Nausea and vomiting have been reported rarely.

Allergic: Anaphylaxis, eosinophilia, itching, drug fever, skin rash, Stevens-Johnson syndrome.

Hematologic: Neutropenia, leukopenia, thrombocytopenia, thrombocythemia.

Hepatic: Transient rise in SGOT, SGPT, and alkaline phosphatase levels has been observed. As with other cephalosporins, reports of hepatitis have been received.

Renal: As with other cephalosporins, reports of increased BUN and creatinine levels, as well as renal failure, have been received.

Local Reactions: Rare instances of phlebitis have been reported at site of injection. Pain at the site of injection after intramuscular administration has occurred infrequently. Some induration has occurred.

Other Reactions: Genital and anal pruritus (including vulvar pruritus, genital moniliasis, and vaginitis).

6.2 Cephalosporin-class Adverse Reactions

In addition to the adverse reactions listed above that have been observed in patients treated with cefazolin, the following adverse reactions and altered laboratory tests have been reported for cephalosporin-class antibacterials: Stevens-Johnson syndrome, erythema multiforme, toxic epidermal necrolysis, renal impairment, toxic nephropathy, aplastic anemia, hemolytic anemia, hemorrhage, hepatic impairment including cholestasis, and pancytopenia.

7 DRUG INTERACTIONS

Probenecid may decrease renal tubular secretion of cephalosporins when used concurrently, resulting in increased and more prolonged cephalosporin blood levels.

8 USE IN SPECIFIC POPULATIONS

8.1 Pregnancy

Pregnancy Category B

Reproduction studies have been performed in rats, mice and rabbits at doses up to 25 times the human dose and have revealed no evidence of impaired fertility or harm to the fetus due to cefazolin. There are, however, no adequate and well-controlled studies in pregnant women. Because animal reproduction studies are not always predictive of human response, this drug should be used during pregnancy only if clearly needed.

8.2 Labor and Delivery

When cefazolin has been administered prior to caesarean section, drug levels in cord blood have been approximately one quarter to one third of maternal drug levels. The drug appears to have no adverse effect on the fetus.

8.3 Nursing Mothers

Cefazolin for Injection is present in very low concentrations in the milk of nursing mothers. Caution should be exercised when Cefazolin for Injection is administered to a nursing woman.

8.4 Pediatric Use

Safety and effectiveness for use in premature infants and neonates have not been established. See Dosage and Administration (2.4) for recommended dosage in pediatric patients older than 1 month.

8.5 Geriatric Use

Of the 920 subjects who received cefazolin in clinical studies, 313 (34%) were 65 years and over, while 138 (15%) were 75 years and over. No overall differences in safety or effectiveness were observed between these subjects and younger subjects. Other reported clinical experience has not identified differences in responses between the elderly and younger patients, but greater sensitivity of some older individuals cannot be ruled out.

This drug is known to be substantially excreted by the kidney, and the risk of toxic reactions to this drug may be greater in patients with impaired renal function. Because elderly patients are more likely to have decreased renal function, care should be taken in dose selection, and it may be useful to monitor renal function [ see Dosage and Administration (2.3)and Warnings and Precautions (5.2)].

8.6 Patients with Renal Impairment

When cefazolin for injection is administered to patients with low urinary output because of impaired renal function (creatinine clearance less than 55 mL/min.), lower daily dosage is required [ see Dosage and Administration (2.3)and Warnings and Precautions (5.2)].

11 DESCRIPTION

Cefazolin for Injection, USP is a semi-synthetic cephalosporin for parenteral administration. It is the sodium salt of 3-{[(5-methyl-1,3,4-thiadiazol-2-yl)thio]-methyl}-8-oxo-7-[2-(1H-tetrazol-1-yl)acetamido]-5-thia-1-azabicyclo[4.2.0]oct-2-ene-2-carboxylic acid.

Structural Formula:

Cefazolin for Injection, USP is a sterile white or off-white powder or crystalline powder.

The sodium contect is 48 mg (2 mEq sodium ion) per 1 gram of cefazolin.

12 CLINICAL PHARMACOLOGY

12.1 Mechanism of Action

Cefazolin is an antibacterial drug [ see Microbiology (12.4)].

12.2 Pharmacodynamics

The pharmacokinetic/pharmacodynamic relationship for cefazolin has not been evaluated in patients.

12.3 Pharmacokinetics

After intramuscular administration of Cefazolin for Injection to normal volunteers, the mean serum concentrations were 37 mcg/mL at 1 hour and 3 mcg/mL at 8 hours following a 500 mg dose, and 64 mcg/mL at 1 hour and 7 mcg/mL at 8 hours following a 1-gram dose.

Studies have shown that following intravenous administration of Cefazolin for Injection to normal volunteers, mean serum concentrations peaked at approximately 185 mcg/mL and were approximately 4 mcg/mL at 8 hours for a 1 gram dose.

The serum half-life for Cefazolin for Injection is approximately 1.8 hours following IV administration and approximately 2 hours following IM administration.

In a study (using normal volunteers) of constant intravenous infusion with dosages of 3.5 mg/kg for 1 hour (approximately 250 mg) and 1.5 mg/kg the next 2 hours (approximately 100 mg), Cefazolin for Injection produced a steady serum level at the third hour of approximately 28 mcg/mL.

Studies in patients hospitalized with infections indicate that Cefazolin for Injection produces mean peak serum levels approximately equivalent to those seen in normal volunteers.

Bile levels in patients without obstructive biliary disease can reach or exceed serum levels up to 5 times; however, in patients with obstructive biliary disease, bile levels of Cefazolin for Injection are considerably lower than serum levels (< 1 mcg/mL).

In synovial fluid, the level of Cefazolin for Injection becomes comparable to that reached in serum at about 4 hours after drug administration.

Studies of cord blood show prompt transfer of Cefazolin for Injection across the placenta. Cefazolin for Injection is present in very low concentrations in the milk of nursing mothers.

Cefazolin for Injection is excreted unchanged in the urine. In the first 6 hours approximately 60% of the drug is excreted in the urine and this increases to 70% to 80% within 24 hours. Cefazolin for Injection achieves peak urine concentrations of approximately 2,400 mcg/mL and 4,000 mcg/mL respectively following 500 mg and 1 gram intramuscular doses.

In patients undergoing peritoneal dialysis (2 L/hr.), Cefazolin for Injection produced mean serum levels of approximately 10 and 30 mcg/mL after 24 hours' instillation of a dialyzing solution containing 50 mg/L and 150 mg/L, respectively. Mean peak levels were 29 mcg/mL (range 13 to 44 mcg/mL) with 50 mg/L (3 patients), and 72 mcg/mL (range 26 to 142 mcg/mL) with 150 mg/L (6 patients). Intraperitoneal administration of Cefazolin for Injection is usually well tolerated.

Controlled studies on adult normal volunteers, receiving 1 gram 4 times a day for 10 days, monitoring CBC, SGOT, SGPT, bilirubin, alkaline phosphatase, BUN, creatinine, and urinalysis, indicated no clinically significant changes attributed to Cefazolin for Injection.

12.4 Microbiology

Mechanism of Action

Cefazolin is a bactericidal agent that acts by inhibition of bacterial cell wall synthesis.

Mechanism of Resistance

Predominant mechanisms of bacterial resistance to cephalosporins include the presence of extended-spectrum beta-lactamases and enzymatic hydrolysis.

Lists of Microorganisms

Cefazolin has been shown to be active against most isolates of the following microorganisms, both in vitro and in clinical infections as described in the Indications and Usage (1) section.

- Gram-Positive Bacteria

Staphylococcus aureus
Staphylococcus epidermidis
Streptococcus pyogenes
Streptococcus agalactiae
Streptococcus pneumoniae

Methicillin-resistant staphylococci are uniformly resistant to cefazolin.

- Gram-Negative Bacteria

Escherichia coli
Proteus mirabilis

Most isolates of indole positive Proteus (Proteus vulgaris), Enterobacter spp., Morganella morganii, Providenciarettgeri, Serratia spp., and Pseudomonas spp . are resistant to cefazolin.

Susceptibility Test Methods

When available, the clinical microbiology laboratory should provide cumulative reports of in vitro susceptibility test results for antimicrobial drug products used in resident hospitals to the physician as periodic reports that describe the susceptibility profile of nosocomial and community-acquired pathogens. These reports should aid the physician in selecting an antibacterial drug product for treatment.

Dilution Techniques

Quantitative methods are used to determine minimum inhibitory concentrations (MICs). These MICs provide estimates of the susceptibility of bacteria to antimicrobial compounds. The MICs should be determined using a standard test^(1, 2) (broth and/or agar). The MIC values obtained should be interpreted according to criteria as provided in Table 4.

Diffusion Techniques

Quantitative methods that require measurement of zone diameters provide reproducible estimates of the susceptibility of bacteria to antimicrobial compounds. The zone size provides an estimate of the susceptibility of bacteria to antimicrobial compounds. The zone size should be interpreted using a standard test method^(2, 3). This procedure uses paper disks impregnated with 30 mcg cefazolin to test the susceptibility of microorganisms to cefazolin. The disk diffusion interpretive criteria are provided in Table 4.

Table 4: Susceptibility Test Interpretive Criteria for Cefazolin [Interpretive criteria are based on 1 g every 8 hr]
Pathogen | Minimum Inhibitory Concentration (mcg/mL) |  |  | Disk Diffusion Zone Diameter (mm)
Pathogen | S | I | R | S | I | R
Enterobacteriaceae | ≤1 | 2 | ≥4 | - | - | -
Abbreviations: S= susceptible, I= intermediate, R= resistant

NOTE:

S. pyogenes and S. agalactiae that have a penicillin MIC of ≤0.12 mcg/mL, or disk diffusion zone diameters of ≥24 mm with a 10 mcg penicillin disk, may be interpreted as susceptible to cefazolin. NOTE: Susceptibility of staphylococci to cefazolin may be deduced from testing either cefoxitin or oxacillin.

A report of Susceptible indicates that the antimicrobial is likely to inhibit growth of the pathogen if the antimicrobial compound reaches the concentrations at the infection site necessary to inhibit growth of the pathogen. A report of Intermediate indicates that the result should be considered equivocal, and, if the microorganism is not fully susceptible to alternative, clinically feasible drugs, the test should be repeated. This category implies possible clinical applicability in body sites where the drug product is physiologically concentrated or in situations where a high dosage of the drug product can be used. This category also provides a buffer zone that prevents small uncontrolled technical factors from causing major discrepancies in interpretation. A report of Resistant indicates that the antimicrobial is not likely to inhibit growth of the pathogen if the antimicrobial compound reaches the concentrations usually achievable at the infection site; other therapy should be selected.

Quality Control

Standardized susceptibility test procedures require the use of laboratory controls to monitor and ensure the accuracy and precision of supplies and reagents used in the assay, and the techniques of the individual performing the test^(1, 2, 3). Standard cefazolin powder should provide the following MIC values noted in Table 5. For the diffusion technique using the 30 mcg disk, the criteria in Table 5 should be achieved.

Table 5: Acceptable Quality Control Ranges for Cefazolin
Quality Control Strain | Minimum Inhibitory Concentration mcg/mL | Disk Diffusion Zone Diameters (mm)
E. coli ATCC® 25922 | 1 to 4 | 21 to 27
S. aureus ATCC® 29213 | 0.25 to 1 | ------------
S. aureus ATCC® 25923 | ------------- | 29 to 35

13 NONCLINICAL TOXICOLOGY

13.1 Carcinogenesis, Mutagenesis, Impairment of Fertility

Mutagenicity studies and long-term studies in animals to determine the carcinogenic potential of Cefazolin for Injection have not been performed.

15 REFERENCES

1. Clinical and Laboratory Standards Institute (CLSI). Methods for Dilution Antimicrobial Susceptibility Tests for Bacteria that Grow Aerobically; Approved Standard – Tenth Edition. CLSI document M07-A10, Clinical and Laboratory Standards Institute, 950 West Valley Road, Suite 2500, Wayne, Pennsylvania 19087, USA, 2015.
2. Clinical and Laboratory Standards Institute (CLSI). Performance Standards for Antimicrobial Susceptibility Testing; Twenty-fifth Informational Supplement, CLSI document M100-S25, Clinical and Laboratory Standards Institute, 950 West Valley Road, Suite 2500, Wayne, Pennsylvania 19087, USA, 2015.
3. Clinical and Laboratory Standards Institute (CLSI). Performance Standards for Antimicrobial Disk Diffusion Susceptibility Tests; Approved Standard – Twelfth Edition. CLSI document M02-A12, Clinical and Laboratory Standards Institute, 950 West Valley Road, Suite 2500, Wayne, Pennsylvania 19087, USA, 2015.

16 HOW SUPPLIED/STORAGE AND HANDLING

Cefazolin for Injection, USP is supplied as a sterile white or off-white powder or crystalline powder. Each vial contains cefazolin sodium equivalent to 1 gram of cefazolin.

Unit of Sale | Strength | Each
NDC 60505-6142-5 Carton containing 25 | 1 Gram | NDC 60505-6142-0 Vial

As with other cephalosporins, cefazolin tends to darken depending on storage conditions; within the stated recommendations, however, product potency is not adversely affected.

Before reconstitution protect from light and store at 20° to 25°C (68° to 77°F) [See USP Controlled Room Temperature].

17 PATIENT COUNSELING INFORMATION

Patients should be advised that allergic reactions, including serious allergic reactions could occur and that serious reactions require immediate treatment and discontinuation of cefazolin. Patients should report to their health care provider any previous allergic reactions to cefazolin, cephalosporins, penicillins, or other similar antibacterials.

Patients should be advised that diarrhea is a common problem caused by antibiotics, which usually ends when the antibiotic is discontinued. Sometimes after starting treatment with antibacterials, patients can develop watery and bloody stools (with or without stomach cramps and fever) even as late as two or more months after having taken the last dose of the antibacterials. If this occurs, patients should contact a physician as soon as possible.

Patients should be counseled that antibacterial drugs, including Cefazolin for Injection should only be used to treat bacterial infections. They do not treat viral infections (e.g., the common cold). When Cefazolin for Injection is prescribed to treat a bacterial infection, patients should be told that although it is common to feel better early in the course of therapy, the medication should be taken exactly as directed. Skipping doses or not completing the full course of therapy may (1) decrease the effectiveness of the immediate treatment and (2) increase the likelihood that bacteria will develop resistance and will not be treatable by Cefazolin for Injection or other antibacterial drugs in the future.

ATCC is a registered trademark of American Type Culture Collection.
Clinitest is a registered trademark of Siemens Medical Solutions Diagnostics.
Clinistix is a registered trademark of Bayer Healthcare LLC.

Manufactured by:

Qilu Pharmaceutical Co., Ltd.

High Tech Zone

Jinan, 250101, China

Manufactured for:

Apotex Corp.

Weston, Florida, USA 33326

Code number: 34040001011C

Revised: 10/2017

PRINCIPAL DISPLAY PANEL - VIAL LABEL

Cefazolin for Injection, USP

1 gram/vial

For IM or IV Use

Rx Only

PRINCIPAL DISPLAY PANEL - OUTER PACKAGE

NDC 71872-7141-1

1 - 1 gram Vial

Cefazolin for Injection, USP

1 gram/vial

For Intramuscular or Intravenous Use

PROTECT FROM LIGHT. RETAIN IN CARTON UNTIL TIME OF USE

Rx Only